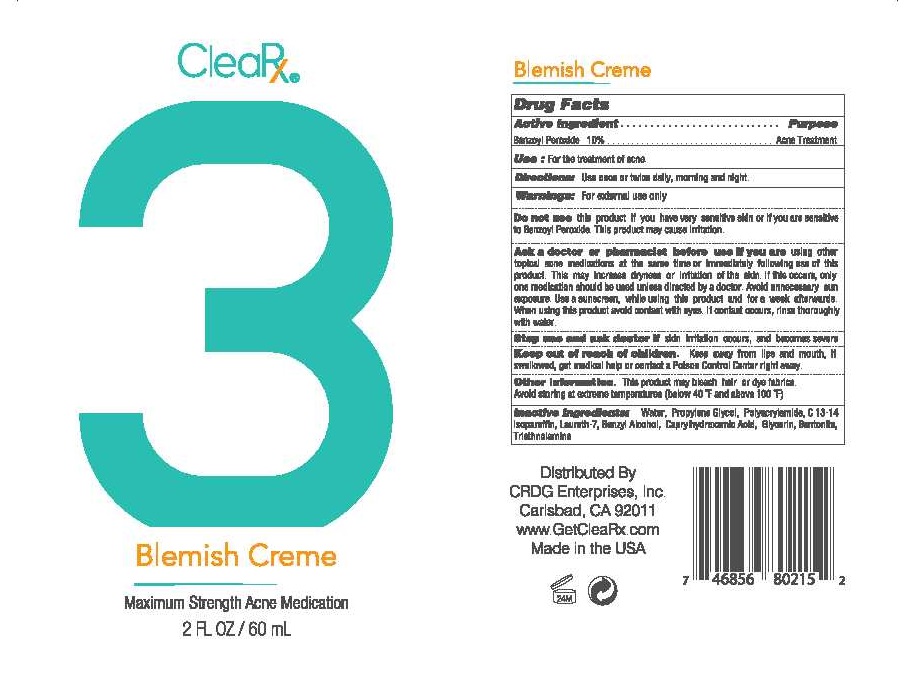 DRUG LABEL: CLEARX 3 BLEMISH CREME
NDC: 71375-101 | Form: CREAM
Manufacturer: CRDG ENTERPRISES INC
Category: otc | Type: HUMAN OTC DRUG LABEL
Date: 20171227

ACTIVE INGREDIENTS: BENZOYL PEROXIDE 10 g/100 mL
INACTIVE INGREDIENTS: WATER; PROPYLENE GLYCOL; POLYACRYLAMIDE (1500 MW); C13-14 ISOPARAFFIN; LAURETH-7; BENZYL ALCOHOL; CAPRYLHYDROXAMIC ACID; GLYCERIN; BENTONITE; TROLAMINE

CLEARX 3 BLEMISH CREME 10% BPO

ACTIVE INGREDIENT

BENZOYL PEROXIDE 10%

PURPOSE

ACNE TREATMENT

USE:

FOR THE TREATMENT OF ACNE

DIRECTIONS:

USE ONCE OR TWICE DAILY, MORNING AND NIGHT.

WARNINGS:

FOR EXTERNAL USE ONLY.

DO NOT USE THIS PRODUCT IF YOU HAVE VERY SENSITIVE SKIN OR IF YOU ARE SENSITIVE TO BENZOYL PEROXIDE. THIS PRODUCT MAY CAUSE IRRITATION.

ASK A DOCTOR OR PHARMACIST BEFORE USE IF YOU ARE USING OTHER TOPICAL ACNE MEDICATIONS AT THE SAME TIME OR IMMEDIATELY FOLLOWING USE OF THIS PRODUCT. THIS MAY INCREASE DRYNESS OR IRRITATION OF THE SKIN. IF THIS OCCURS, ONLY ONE MEDICATION SHOULD BE USED UNLESS DIRECTED BY A DOCTOR. AVOID UNNECESSARY SUN EXPOSURE. USE A SUNSCREEN, WHILE USING THIS PRODUCT AND FOR A WEEK AFTERWARDS.

STOP USE AND ASK A DOCTOR IF SKIN IRRITATION OCCURS, AND BECOMES SEVERE.

KEEP OUT OF REACH OF CHILDREN. KEEP AWAY FROM LIPS AND MOUTH. IF SWALLOWED, GET MEDICAL HELP OR CONTACT THE POISON CONTROL CENTER RIGHT AWAY.

OTHER INFORMATION.

THIS PRODUCT MAY BLEACH HAIR OR DYE FABRICS. AVOID STORING AT EXTREME TEMPERATURES (BELOW 40°F AND ABOVE 100°F).

INACTIVE INGREDIENTS:

WATER, PROPYLENE GLYCOL, POLYACRYLAMIDE, C 13-14 ISOPARAFFIN, LAURETH-7, BENZYL ALCOHOL, CAPRYLHYDROXAMIC ACID, GLYCERIN, BENTONITE, TRIETHANOLAMINE.